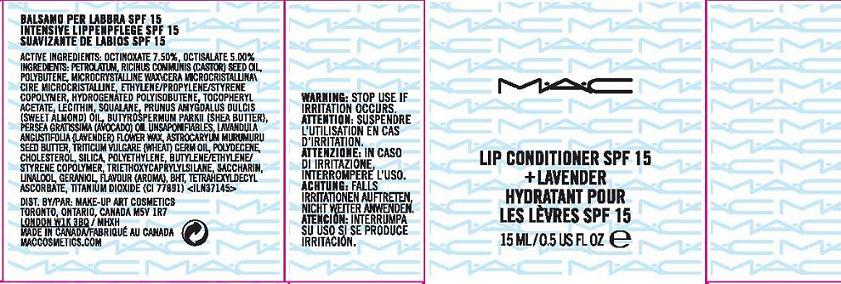 DRUG LABEL: LIP CONDITIONER
NDC: 40046-0040 | Form: GEL
Manufacturer: MAKEUP ART COSMETICS
Category: otc | Type: HUMAN OTC DRUG LABEL
Date: 20101130

ACTIVE INGREDIENTS: OCTINOXATE 7.5 mL/100 mL; OCTISALATE 5.0 mL/100 mL
INACTIVE INGREDIENTS: PETROLATUM; CASTOR OIL; MICROCRYSTALLINE WAX

ACTIVE INGREDIENTS: OCTINOXATE 7.50% [] OCTISALATE 5.00%

INACTIVE INGREDIENT

INACTIVE INGREDIENTS: PETROLATUM [] RICINUS COMMUNIS (CASTOR) SEED OIL [] POLYBUTENE [] MICROCRYSTALLINE WAX\CERA MICROCRISTALLINA\CIRE MICROCRISTALLINE [] ETHYLENE/PROPYLENE/STYRENE COPOLYMER [] HYDROGENATED POLYISOBUTENE [] TOCOPHERYL ACETATE [] LECITHIN [] SQUALANE [] PRUNUS AMYGDALUS DULCIS (SWEET ALMOND) OIL [] BUTYROSPERMUM PARKII (SHEA BUTTER) [] PERSEA GRATISSIMA (AVOCADO) OIL UNSAPONIFIABLES [] LAVANDULA ANGUSTIFOLIA (LAVENDER) FLOWER WAX [] ASTROCARYUM MURUMURU SEED BUTTER [] TRITICUM VULGARE (WHEAT) GERM OIL [] POLYDECENE [] CHOLESTEROL [] SILICA [] POLYETHYLENE [] BUTYLENE/ETHYLENE/STYRENE COPOLYMER [] TRIETHOXYCAPRYLYLSILANE [] SACCHARIN [] LINALOOL [] GERANIOL [] FLAVOUR (AROMA) [] BHT [] TETRAHEXYLDECYL ASCORBATE [] TITANIUM DIOXIDE (CI 77891)

WARNINGS

WARNING: STOP USE IF IRRITATION OCCURS.

PACKAGE LABEL

PRINCIPAL DISPLAY PANEL:

MAC

LIP CONDITIONER SPF 15

+ LAVENDER

15 ML/0.5 US FL OZ.

DISTR. BY MAKEUP ART COSMETICS
TORONTO, ONTARIO, CANADA, M5V 1R7